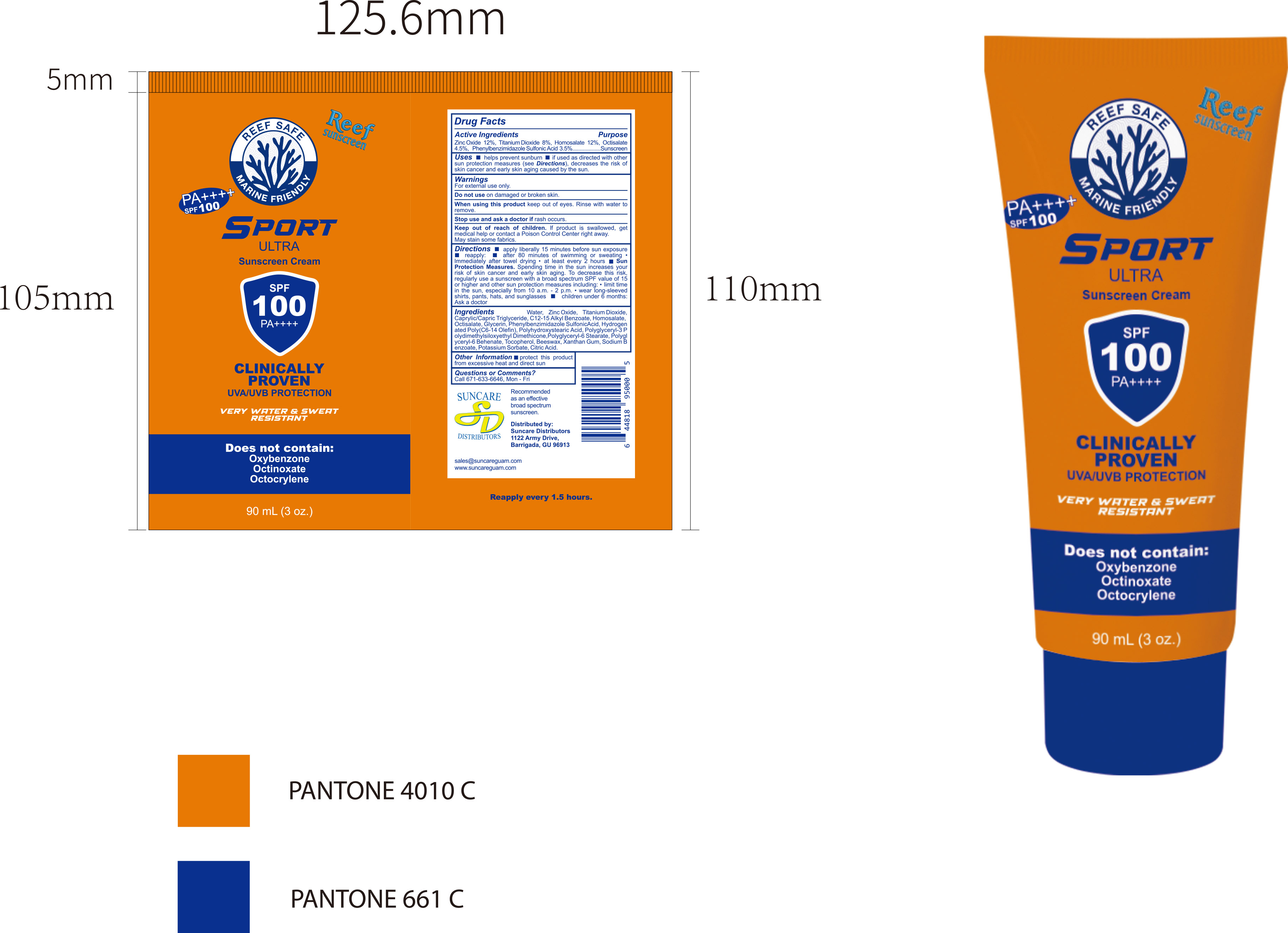 DRUG LABEL: Sunscreen Cream
NDC: 84938-007 | Form: CREAM
Manufacturer: Foshan Sugar Max Cosmetics CO.,Ltd
Category: otc | Type: HUMAN OTC DRUG LABEL
Date: 20251216

ACTIVE INGREDIENTS: PHENYLBENZIMIDAZOLE SULFONIC ACID 0.035 g/1 mL; ZINC OXIDE 0.12 g/1 mL; TITANIUM DIOXIDE 0.08 g/1 mL; HOMOSALATE 0.12 g/1 mL; OCTISALATE 0.045 g/1 mL
INACTIVE INGREDIENTS: BEESWAX; POTASSIUM SORBATE; POLYGLYCERYL-3 POLYDIMETHYLSILOXYETHYL DIMETHICONE (4000 MPA.S); SODIUM BENZOATE; CAPRYLIC/CAPRIC TRIGLYCERIDE; HYDROGENATED POLY(C6-14 OLEFIN; 2 CST); WATER; CITRIC ACID; C12-15 ALKYL BENZOATE; GLYCERIN; POLYHYDROXYSTEARIC ACID (2300 MW); POLYGLYCERYL-6 STEARATE; POLYGLYCERYL-6 BEHENATE; TOCOPHEROL; XANTHAN GUM

84938-007 Sunscreen Cream

ACTIVE INGREDIENT

Zinc Oxide 12%,Titanium Dioxide 8%, Homosalate 12%, Octisalate4.5%,Phenylbenzimidazole Sulfonic Acid 3.5%

PURPOSE

Sunscreen

INDICATIONS AND USAGE

Uses helps prevent sunburn if used as directed with other sun protection measures (see Directions), decreases the risk of skin cancer and early skin aging caused by the sun.

WARNINGS

For external use only.

Do not use on damaged or broken skin.

When using this product keep out of eyes. Rinse with water to remove.

Stop use and ask a doctor if rash occurs

Keep out of reach of children. lf product is swallowed, get medical help or contact a Poison Control Center right away.May stain some fabrics.

DOSAGE AND ADMINISTRATION

Directions apply liberally 15 minutes before sun exposure reapply: after 80 minutes of swimming or sweating Immediately after towel drying "at least every 2 hours Sun Protection Measures, Spending time in the sun increases your risk of skin cancer and early skin aging. To decrease this risk,regularly use a sunscreen with a broad spectrum SPF value of 15 or higher and other sun protection measures including:" limit timein the sun,especially from 10 a.m.-2 p.m."wear long-sleeved children under 6 months: shirts, pants, hats, and sunglassesAsk a doctor

INACTIVE INGREDIENT

Aqua (Water)
Caprylic/Capric Triglyceride
C12‑15 Alkyl Benzoate
Glycerin
Hydrogenated Poly(C6‑14 Olefin)
Polyhydroxystearic Acid
Polyglyceryl‑3 Polydimethylsiloxyethyl Dimethicone
Polyglyceryl‑6 Stearate
Polyglyceryl‑6 Behenate
Tocopherol
Beeswax
Xanthan Gum
Sodium Benzoate
Potassium Sorbate
Citric Acid